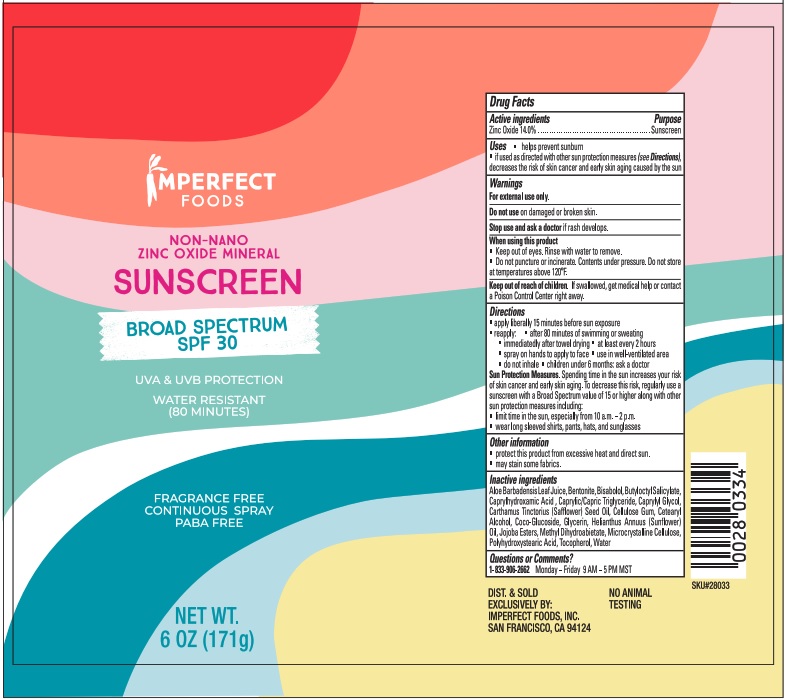 DRUG LABEL: Sunscreen
NDC: 81757-002 | Form: SPRAY
Manufacturer: Imperfect Foods
Category: otc | Type: HUMAN OTC DRUG LABEL
Date: 20210426

ACTIVE INGREDIENTS: ZINC OXIDE 14 g/100 g
INACTIVE INGREDIENTS: ALOE VERA LEAF; BENTONITE; LEVOMENOL; BUTYLOCTYL SALICYLATE; CAPRYLHYDROXAMIC ACID; MEDIUM-CHAIN TRIGLYCERIDES; CAPRYLYL GLYCOL; SAFFLOWER OIL; CARBOXYMETHYLCELLULOSE SODIUM; CETOSTEARYL ALCOHOL; COCO GLUCOSIDE; GLYCERIN; SUNFLOWER OIL; JOJOBA OIL, RANDOMIZED; METHYL DIHYDROABIETATE; MICROCRYSTALLINE CELLULOSE; POLYHYDROXYSTEARIC ACID (2300 MW); TOCOPHEROL; WATER

Active Ingredients

Zinc Oxide 14%

Uses

- Helps prevent sunburn
- If used as directed with other sun protection measures (see Directions) decreases the risk of skin cancer and early skin aging caused by the sun

Warnings

For external use only

Do not use

On damaged or broken skin

Ask Doctor

Stop use and ask a doctor if rash develops

When using

- When using this product keep out of eyes. Rinse with water to remove.
- Do not puncture or incinerate. Contents under pressure. Do not store at temperatures above 120 degrees F.

Keep out of reach of children. If swallowed, get medical help or contact a Poison Control Center right away.

Directions

- Apply liberally 15 minutes before sun exposure
- reapply: after 80 minutes of swimming or sweating
- immediately after towel drying
- at least every 2 hours
- Spray on hands and apply to face
- use in well-ventilated area
- do not inhale
- children under 6 months: ask a doctor

Sun Protection Measures. Spending time in the sun increases your risk of skin cancer and early skin aging. To decrease this risk, regularly use a sunscreen with Broad Spectrum value of 15 or higher along with other sun protection measures including:

- limit time in the sun, especially from 10a.m. - 2 p.m.
- wear long sleeved shirts, pants, hats and sunglasses

Other Information

- Protect this product from excessive heat and direct sun
- may stain some fabrics

Inactive Ingredients

Aloe Barbadensis Leaf Juice, Bentonite, Bisabolol, Butyloctyl Salicylate, Caprylhydroxamic Acid , Caprylic/Capric Triglyceride, Caprylyl Glycol, Carthamus Tinctorius (Safflower) Seed Oil, Cellulose Gum, Cetearyl Alcohol, Coco-Glucoside, Glycerin, Helianthus Annuus (Sunflower) Oil, Jojoba Esters, Methyl Dihydroabietate, Microcrystalline Cellulose, Polyhydroxystearic Acid, Tocopherol, Water.

Questions or Comments?

1-833-909-2662 Monday - Friday 9am-5pm MST

PACKAGE LABEL

SPF 30 Sunscreen Spray NDC: 81757-002-06